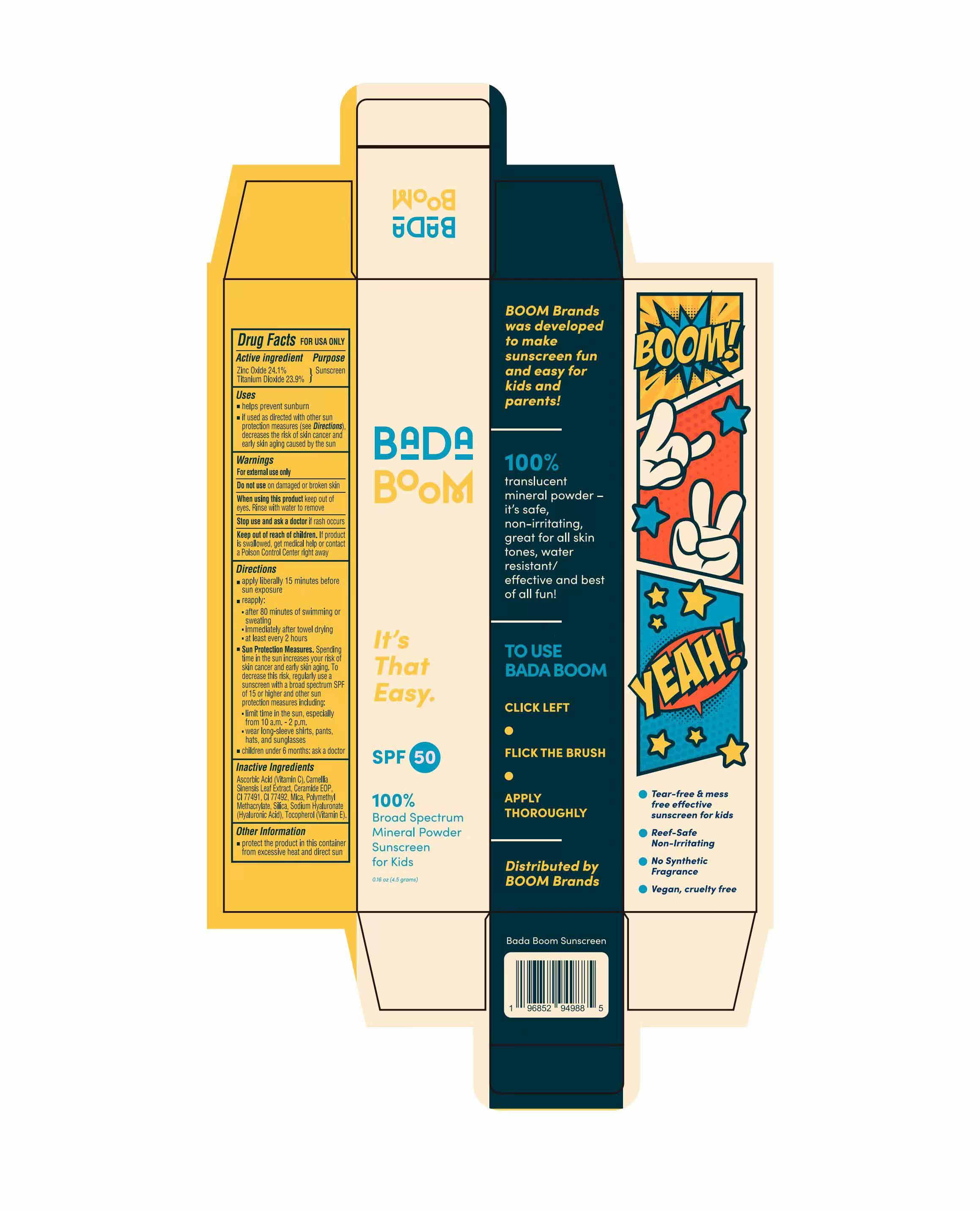 DRUG LABEL: BadaBOOM Sunscreen
NDC: 82723-002 | Form: CREAM
Manufacturer: Aopline Health Industry Technology (Guangzhou) Co., Ltd.
Category: otc | Type: HUMAN OTC DRUG LABEL
Date: 20250108

ACTIVE INGREDIENTS: ZINC OXIDE 24.1 g/100 g; TITANIUM DIOXIDE 23.9 g/100 g
INACTIVE INGREDIENTS: CERAMIDE NP; HYALURONATE SODIUM; ETHYL ACRYLATE AND METHYL METHACRYLATE COPOLYMER DISPERSION (2:1; 600000 MW 30% AQUEOUS); .ALPHA.-TOCOPHEROL CALCIUM SUCCINATE, DL-

82723-002
BadaBOOM Sunscreen

Active Ingredients

Zinc Oxide 24.1%
Titanium Dioxide 23.9%

Purpose

Sunscreen

Uses

helps prevent sunburn
if used as directed with other sun protection measures (see Directions)decreases the risk of skin cancer and early skin aging caused by the sun

Warnings

For external use only.
Do not use on damaged or broken skin.
When using this product keep out of eyes. Rinse with water to remove.
Stop use and ask a doctor if rash occurs.
Keep out of reach of children. If product is swallowed , get medical help or contact a Poison Control Center right away.

Directions

apply liberally 15 minutes before sun exposure.
reapply :after 80 minutes of swimming or sweating.
immediately after towel drying.
at least every 2 hours.
Sun Protection Measures. Spending time in the sun increases your risk of skin cancer and early skin aging. To decrease this risk, regularly use a sunscreen with a broad spectrum SPF of 15 or higher and other sun protection measures including:
limit time in the sun, especially from 10 a m. -2 p.m.
wear long-sleeve shirts, pants, hats, and sunglasses.
children under 6 months: ask a doctor.

Other Information

protect the product in this container from excessive heat and direct sun

Inactive Ingredients

Ascorbic Acid (Vitamin C) , Camellia Sinensis Leaf Extract , Ceramide EOP, CI 77491 , CI 77492 , Mica , Polymethyl Methacrylate , Silica , Sodium Hyaluronate(Hyaluronic Acid) , Tocopherol (Vitamin E)

Keep out of reach of children. If product is swallowed , get medical help or contact a Poison Control Center right away.

Stop use

Stop use and ask a doctor if rash occurs.

When using this product keep out of eyes. Rinse with water to remove.
Stop use and ask a doctor if rash occurs.
Keep out of reach of children. If product is swallowed , get medical help or contact a Poison Control Center right away.

Do not use on damaged or broken skin.

Package Label

82723-002-01